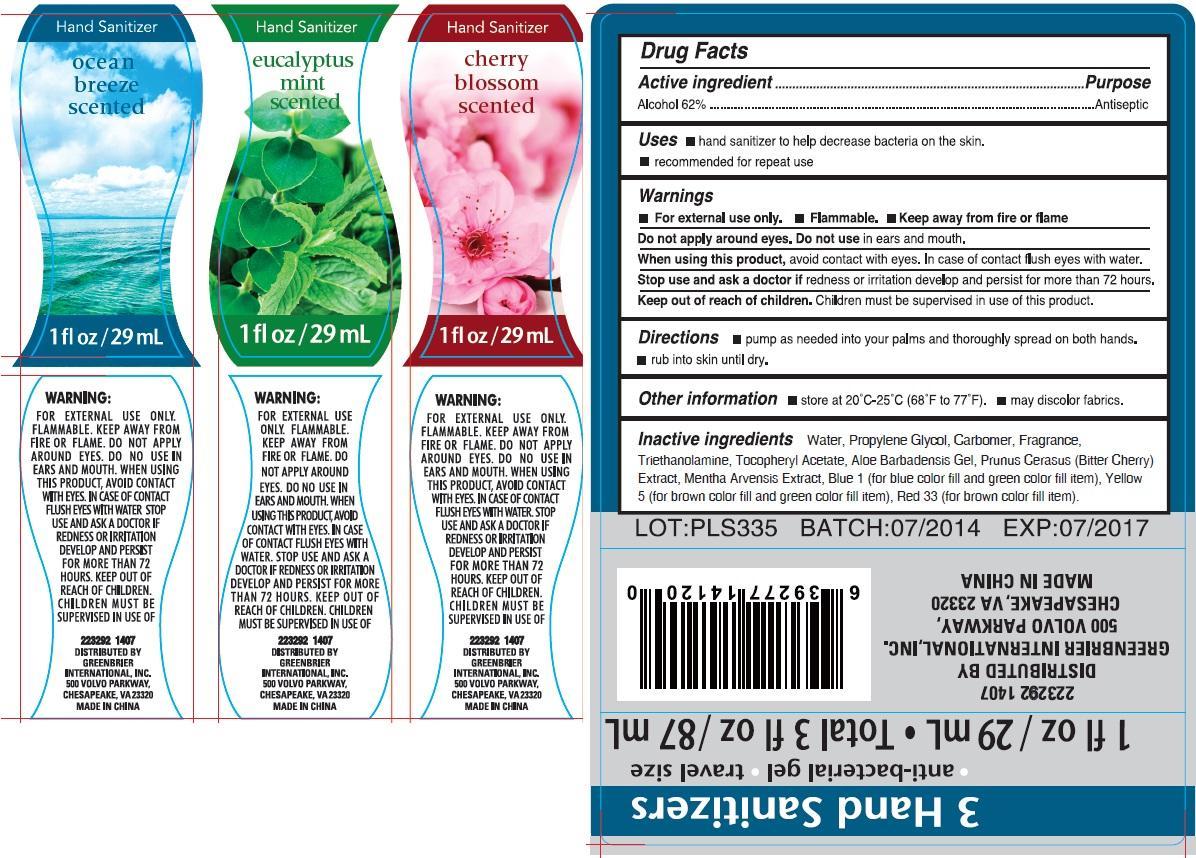 DRUG LABEL: 3 Hand Sanitizers
NDC: 40104-330 | Form: KIT | Route: TOPICAL
Manufacturer: Ningbo Pulisi Daily Chemical Products Co.,Ltd.
Category: otc | Type: HUMAN OTC DRUG LABEL
Date: 20150122

ACTIVE INGREDIENTS: ALCOHOL 62 mL/100 mL; ALCOHOL 62 mL/100 mL; ALCOHOL 62 mL/100 mL
INACTIVE INGREDIENTS: ISOPROPYL MYRISTATE; CARBOMER 940; FD&C BLUE NO. 1; D&C RED NO. 33; FD&C YELLOW NO. 5; GLYCERIN; PROPYLENE GLYCOL; WATER; ISOPROPYL MYRISTATE; CARBOMER 940; FD&C BLUE NO. 1; D&C RED NO. 33; FD&C YELLOW NO. 5; GLYCERIN; PROPYLENE GLYCOL; WATER; ISOPROPYL MYRISTATE; CARBOMER 940; FD&C BLUE NO. 1; D&C RED NO. 33; FD&C YELLOW NO. 5; GLYCERIN; PROPYLENE GLYCOL; WATER

3 Hand Sanitizers - Anti-bacterial gel - travel size

Active Ingredient

Alcohol 62%

Purpose

Antiseptic

Uses

- Hand sanitizer to help decrease bacteria on the skin
- recommended for repeat use

Warnings

For External use only. Flammable. Keep away from fire or flame

Do not apply around eyes, do not use in ears and mouth.

When using this product

avoid contact with eyes. In case of contact flush eyes with water.

Stop use and ask a doctor

if redness or irritation develop and persist for more than 72 hours

Keep out or reach of children.

Children must be supervised in use of this product.

Directions

- Pump as needed into your palms and thoroughly spread on both hands.
- rub into skin until dry.

Other information

store at 20C-25C (68F to 77F)

May discolor fabrics

Inactive Ingredients

Aloe barbadensis gel, Carbomer, FDandC Blue No. 1 (for blue color fill item), FDandC Red No. 33, FDandC Yellow No. 5 (for brown color fill item), Fragrance, Glycerin, isopropyl myristate, Propylene glycol, tocopheryl acetate, triethanolamine, Water.

DESCRIPTION

3 Hand Sanitizers

Antibacterial gel - travel size

1fl oz/29ml - Total 3fl oz / 87mL

121403 1311

Made in China
Distributed by
Greenbrier International, Inc. 500 Volvo Parkway, Chesapeake VA 23320